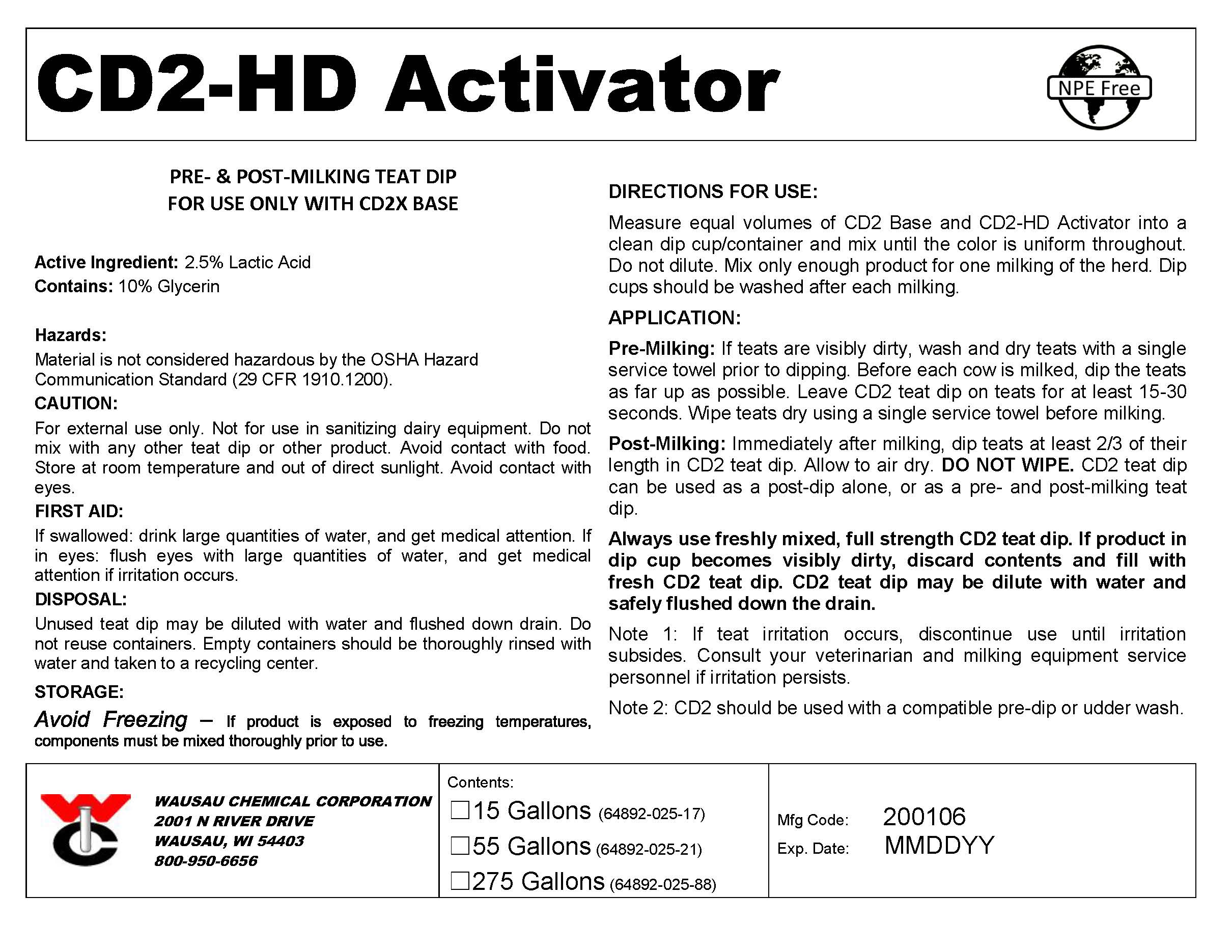 DRUG LABEL: CD2-HD Activator
NDC: 64892-025 | Form: SPRAY, METERED
Manufacturer: Wausau Chemical
Category: animal | Type: OTC ANIMAL DRUG LABEL
Date: 20200106

ACTIVE INGREDIENTS: LACTIC ACID 25 mg/1 L

Disposal:

Unused teat dip may be diluted with water and flushed down drain. Do not reuse containers. Empty containers should be thoroughly rinsed with water and taken to a recycling center.

GENERAL PRECAUTIONS

Material is not considered hazardous by the OSHA Hazard Communication Standard (29 CFR 1910.1200).

First Aid:

IF SWALLOWED: drink large quantities of water and get medical attention.

IF IN EYES: flush eyes with large quantities of water and get medical attention if irritation occurs..

Handling Instructions:

For external use only. Not for use in sanitizing dairy equipment. Avoid contact with eyes. Avoid contact with food.

Storage & Handling:

Do not mix with any other teat dip or other product. Store at room temperature and out of direct sunlight.

Avoid freezing - If product is exposed to freezing temperatures, components must be mixed thoroughly prior to use.

DIRECTIONS:

Measure equal volumes of CD2 Base and CD2-HD Activator into a clean dip cup/container and mix until the color is uniform throughout. Do not dilute. Mix only enough product for one milking of the herd. Dip cups should be washed after each milking.

APPLICATION:

Pre-Milking: If teats are visibly dirty, wash and dry teats with a single service towel prior to dipping. Before each cow is milked, dip the teats as far up as possible. Leave CD2 teat dip on teats for at least 15-30 seconds. Wipe teats dry using a single service towel before milking.

Post-Milking: Immediately after milking, dip teats at least 2/3 of their length in CD2 teat dip. Allow to air dry. DO NOT WIPE. CD2 teat dip can be used as a post-dip alone, or as a pre- and post-milking teat dip.

Always use freshly mixed, full strength CD2 teat dip. If product in dip cup becomes visibly dirty, discard contents and fill with fresh CD2 teat dip. CD2 teat dip may be diluted with water and safely flushed down the drain.

Note 1: If teat irritation occurs, discontinue use until irritation subsides. Consult your veterinarian and milking equipment service personnel if irritation persists.

Note 2: CD2 should be used with a compatible pre-dip or udder wash.

Active Ingredient:
Lactic Acid.....................................................................................2.5%

Inactive Ingredients:
Glycerin.......................................................................................10.0%
Surfactants, water.......................................................................87.5%

Wausau Chemical Corporation

2001 N River Drive

Wausau, WI 54403

800-950-6656